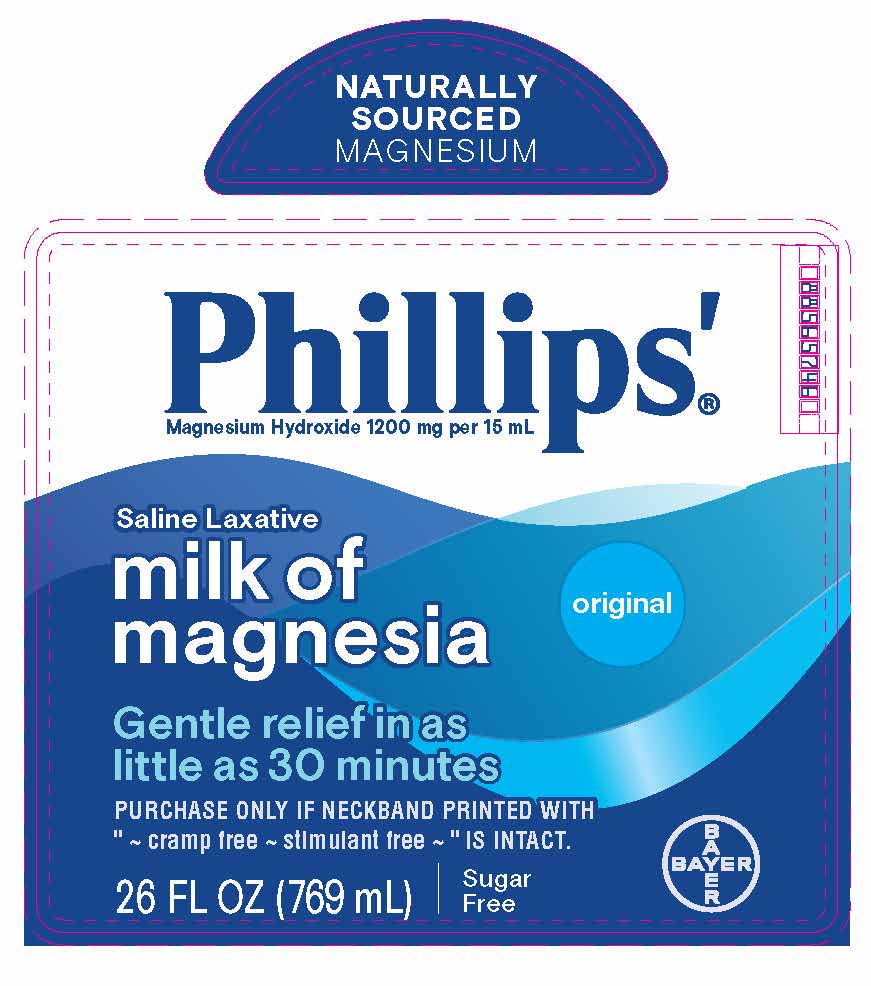 DRUG LABEL: PHILLIPS ORIGINAL MILK OF MAGNESIA
NDC: 0280-0030 | Form: LIQUID
Manufacturer: Bayer HealthCare LLC.
Category: otc | Type: HUMAN OTC DRUG LABEL
Date: 20251204

ACTIVE INGREDIENTS: MAGNESIUM HYDROXIDE 1200 mg/15 mL
INACTIVE INGREDIENTS: WATER; SODIUM HYPOCHLORITE

Phillips’ Milk of Magnesia-Original

Drug Facts

Active ingredient (in each 15 mL)

Magnesium hydroxide 1200 mg

PURPOSE

Saline laxative

Use

Use relieves occasional constipation (irregularity). This product usually produces bowel movement in ½ to 6 hours.

Warnings

Do not use if you have ever had an allergic reaction to this product or any of its ingredients.

Ask a doctor before use if you have

● kidney disease
● a magnesium-restricted diet
● stomach pain, nausea, or vomiting
● a sudden change in bowel habits that lasts over 14 days

Ask a doctor or pharmacist before use if you are taking a prescription drug. This product may interact with certain prescription drugs.

Stop use and ask a doctor if

● you have rectal bleeding or no bowel movement after using this product. These could be signs of a serious condition.

● you need to use a laxative for more than 1 week

PREGNANCY OR BREAST FEEDING

If pregnant or breast-feeding, ask a health professional before use.

Keep out of reach of children. In case of overdose, get medical help or contact a Poison Control Center right away.

Directions

● do not exceed the maximum recommended daily dose in a 24 hour period

● shake well before use

● dose may be taken once a day preferably at bedtime, in divided doses, or as directed by a doctor. Drink a full glass (8 oz) of liquid with each dose.

● for accurate dosing, only use the dosing cup provided

● mL = milliliter

adults and children 12 years and older | 30 mL to 60 mL
children 6 to 11 years | 15 mL to 30 mL
children under 6 years | ask a doctor

Other information

● each (15 mL) contains: magnesium 500 mg

● store at room temperature. Avoid excessive heat above 40°C (104°F). Avoid freezing. Close cap tightly after use.

Inactive ingredients purified water, sodium hypochlorite

Questions or comments? 1-800-986-0369 (Mon – Fri 9AM – 5PM EST)